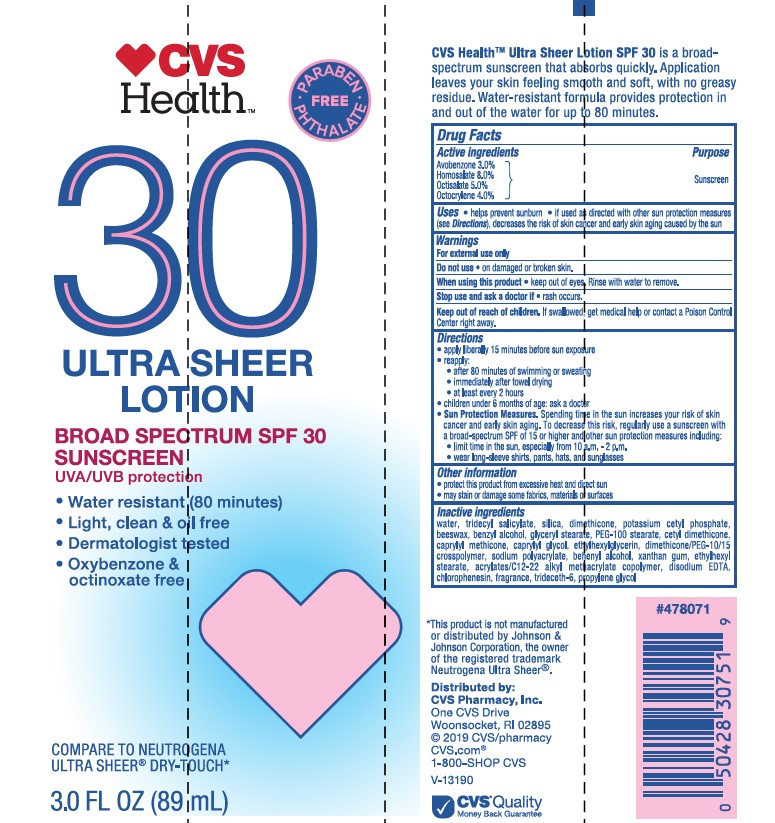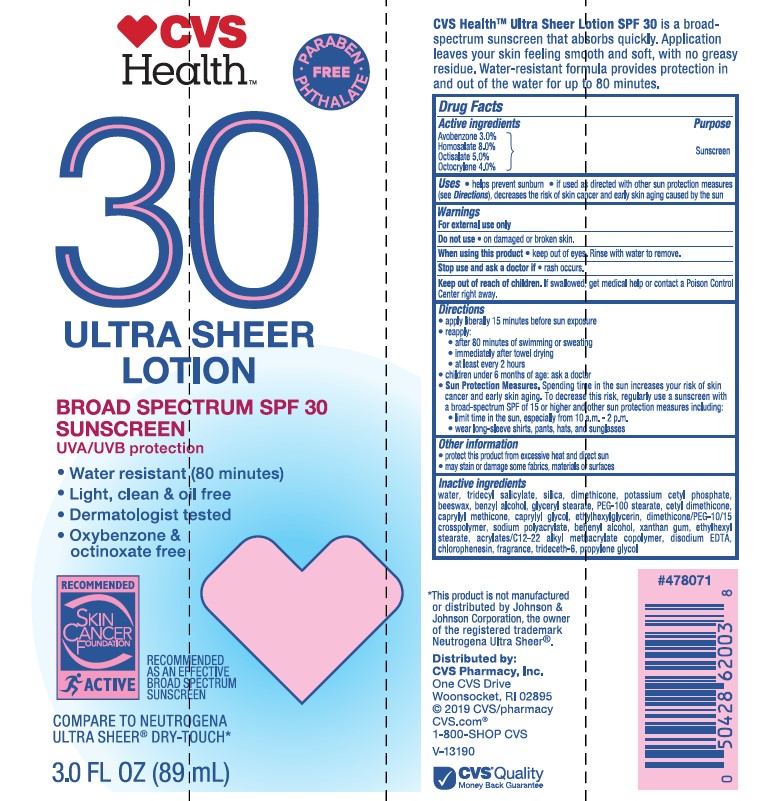 DRUG LABEL: CVS Health SPF 30 Ultra Sheer
NDC: 51316-029 | Form: LOTION
Manufacturer: CVS PHARMACY
Category: otc | Type: HUMAN OTC DRUG LABEL
Date: 20241017

ACTIVE INGREDIENTS: HOMOSALATE 80 mg/1 mL; OCTOCRYLENE 40 mg/1 mL; AVOBENZONE 30 mg/1 mL; OCTISALATE 50 mg/1 mL
INACTIVE INGREDIENTS: SODIUM POLYACRYLATE (8000 MW); BUTYL ACRYLATE/C16-C20 ALKYL METHACRYLATE/METHACRYLIC ACID/METHYL METHACRYLATE COPOLYMER; CAPRYLYL TRISILOXANE; ETHYLHEXYLGLYCERIN; GLYCERYL 1-STEARATE; POTASSIUM CETYL PHOSPHATE; CHLORPHENESIN; PROPYLENE GLYCOL; DOCOSANOL; DIMETHICONE; CAPRYLYL GLYCOL; PEG-100 STEARATE; ETHYLHEXYL STEARATE; BENZYL ALCOHOL; XANTHAN GUM; CETYL DIMETHICONE 45; SILICON DIOXIDE; WATER; WHITE WAX; TRIDECETH-6; EDETATE DISODIUM; DIMETHICONE/PEG-10/15 CROSSPOLYMER; TRIDECYL SALICYLATE

CVS Health SPF 30 Ultra Sheer Lotion

Active ingredients

Avobenzone 3.0%, Homosalate 8.0%, Octisalate 5.0%, Octocrylene 4.0%

Purpose

Sunscreen

Uses

- helps prevent sunburn
- if used as directed with other sun protection measures (see Directions), decreases the risk of skin cancer and early aging caused by the sun

Warnings

For external use only

Do not use

• on damaged or broken skin.

When using this product

• keep out of eyes. Rinse with water to remove.

Stop use and ask a doctor if

• rash occurs.

Keep out of reach of children.

If swallowed, get medical help or contact a Poison Control Center right away.

Directions

- apply liberally 15 minutes before sun exposure.
- Reapply:
- after 80 minutes of swimming or sweating
- immediately after towel drying
- at least every 2 hours
- children under 6 months of age: Ask a doctor
- Sun Protection Measures. Spending time in the sun increases your risk of skin cancer and early skin aging. To decrease this risk, regularly use a sunscreen with a Broad Spectrum SPF value of 15 or higher and other sun protection measures including:
- limit time in the sun especially from 10 a.m. – 2 p.m.
- wear long-sleeved shirts, pants, hats, and sunglasses

Other information

- protect the product in this container from excessive heat and direct sun
- may stain or damage some fabrics, materials or surfaces

Inactive ingredients

water, tridecyl salicylate, silica, dimethicone, potassium cetyl phosphate, beeswax, benzyl alcohol, glyceryl stearate, PEG-100 stearate, cetyl dimethicone, caprylyl methicone, caprylyl glycol, ethyhexylglycerin, dimethicone/PEG-10/15 crosspolymer, sodium polyacrylate, behenyl alcohol, xanthan gum, ethylhexyl stearate, acrylates/C12-22 alkyl methacrylate copolymer, disodium EDTA, chlorphenesin, fragrance, trideceth-6, propylene glycol